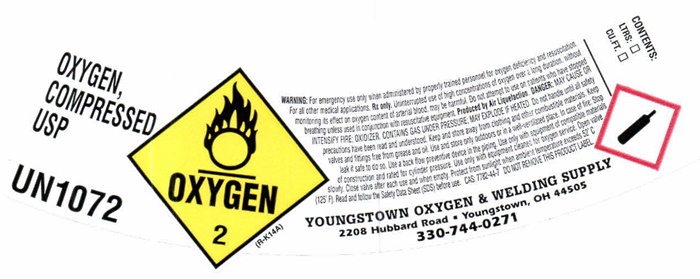 DRUG LABEL: OXYGEN
NDC: 54316-123 | Form: GAS
Manufacturer: Youngstown Oxygen & Welding Supply, Inc.
Category: prescription | Type: HUMAN PRESCRIPTION DRUG LABEL
Date: 20241029

ACTIVE INGREDIENTS: OXYGEN .995 L/1 L

Oxygen - 123

OXYGEN, COMPRESSED product label

OXYGEN, COMPRESSED USP UN 1072 OXYGEN 2 (R-K14A)

WARNING: For emergency use only when administered by properly trained personnel for oxygen deficiency and resuscitation. For all other medical applications, Rx only. Uninterrupted use of high concentrations of oxygen over a long duration, without monitoring its effect on oxygen content of arterial blood, may be harmful. Do not attempt to use on patients who have stopped breathing unless used in conjunction with resuscitative equipment. Produced by Air Liquefaction. DANGER: MAY CAUSE OR INTENSIFY FIRE; OXIDIZER. CONTAINS GAS UNDER PRESSURE; MAY EXPLODE IF HEATED. Do not handle until all safety precautions have been read and understood. Keep and store away from clothing and other combustible materials. Keep valves and fittings free from grease and oil. Use and store only outdoors or in a well-ventilated place. In case of fire: Stop leak if safe to do so. Use a back flow preventive device in the piping. Use only with equipment of compatible materials of construction and rated for cylinder pressure. Use only with equipment cleaned for oxygen service. Open valve slowly. Close valve after each use and when empty. Protect from sunlight when ambient temperature exceeds 52°C (125° F). Read and follow the Safety Data Sheet (SDS) before use. CAS 7782-44-7 DO NOT REMOVE THIS PRODUCT LABEL.

CONTENTS:

LTRS: ___

CU.FT. ___

YOUNGSTOWN OXYGEN & WELDING SUPPLY

2208 Hubbard Road • Youngstown, OH 4505

330-744-0271